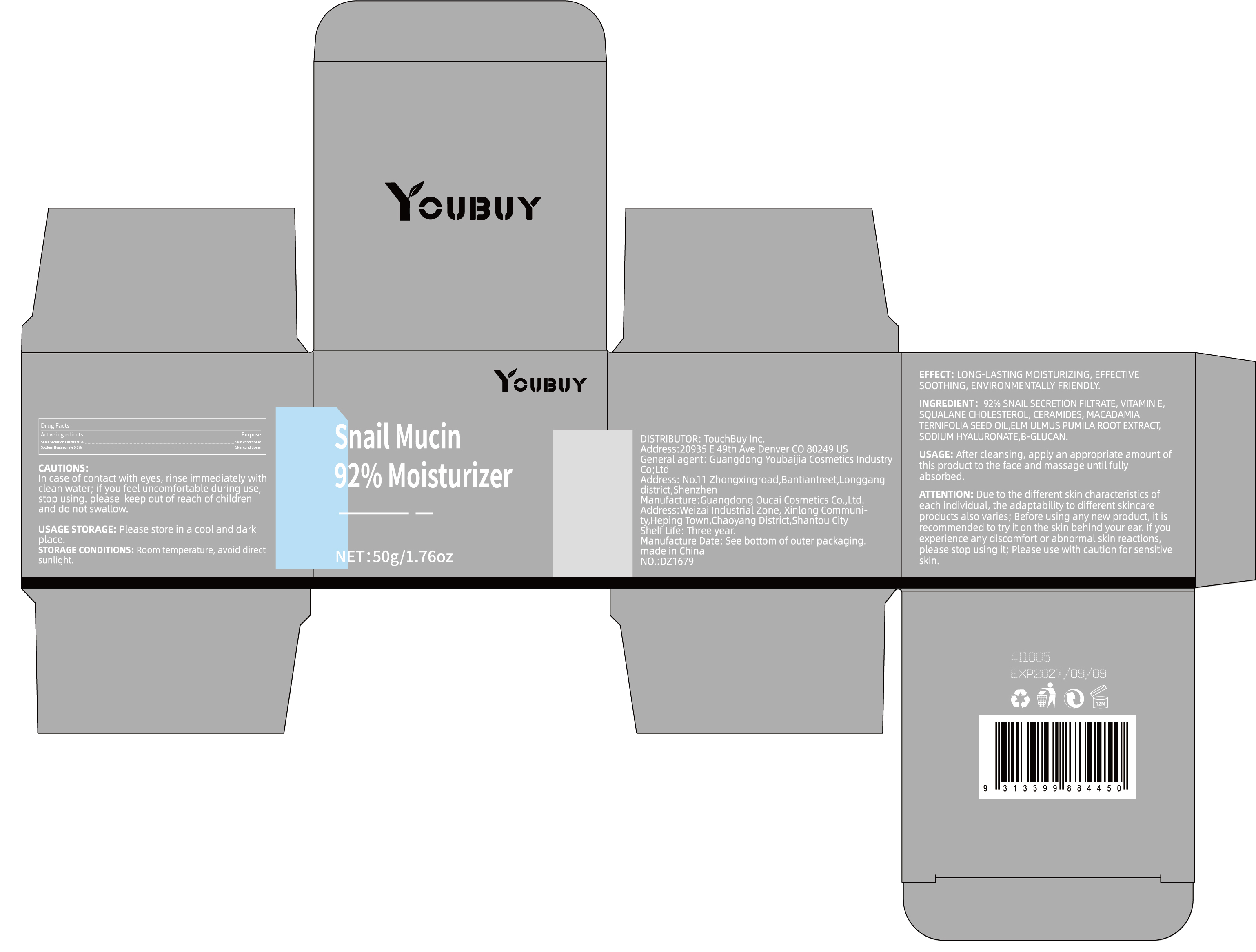 DRUG LABEL: YOUBUY Snail Mucin 92% Moisturizer
NDC: 84712-034 | Form: CREAM
Manufacturer: Guangdong Youbaijia Cosmetic Industry Co., Ltd
Category: otc | Type: HUMAN OTC DRUG LABEL
Date: 20241127

ACTIVE INGREDIENTS: SODIUM HYALURONATE 0.05 g/50 g; SNAIL SECRETION FILTRATE 46 g/50 g
INACTIVE INGREDIENTS: CHOLESTEROL 0.6 g/50 g

ACTIVE INGREDIENT

Snail Secretion Filtrate 92%
Sodium Hyaluronate 0.1%

DO NOT USE

on damaged or broken skin

Keep away from children. Do not swallow.

PURPOSE

LONG-LASTING MOISTURIZING

QUESTIONS

Contact name: Jessie Peng
Company phone number: +1 818 579 7288
Company e-mail: jessie@registeragentllc.com

STOP USE

lf skin becomes red or irritated, discontinue use immediately and wash with water.

WHEN USING

keep out of eyes. Rinse with water to remove.

WARNINGS

For external use only.

INACTIVE INGREDIENT

VITAMIN E, SQUALANE CHOLESTEROL, CERAMIDES, MACADAMIA TERNIFOLIA SEED OIL,ELM ULMUS PUMILA ROOT EXTRACT,B-GLUCAN.

DOSAGE AND ADMINISTRATION

After cleansing, apply an appropriate amount of this product to the face and massage until fully absorbed.

INDICATIONS AND USAGE

LONG-LASTING MOISTURIZING, EFFECTIVE SOOTHING,ENVIRONMENTALLY FRIENDLY.

STORAGE AND HANDLING

Keep away from light and in a dry place.